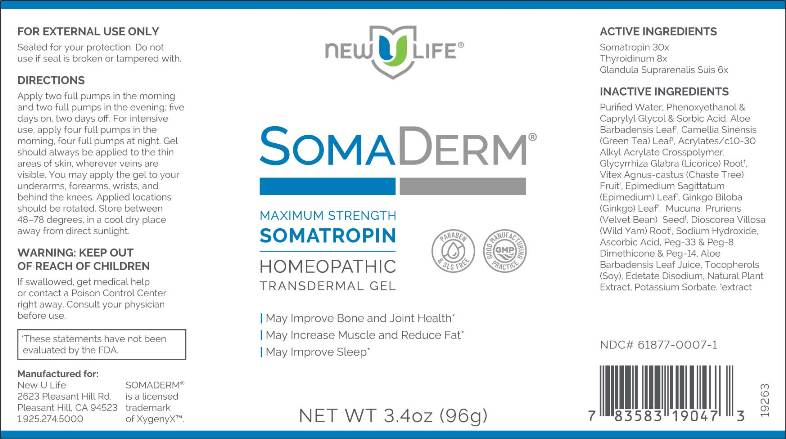 DRUG LABEL: Somaderm
NDC: 61877-0007 | Form: GEL
Manufacturer: Natural Life Foods Corporation dba XYGENYX
Category: homeopathic | Type: HUMAN OTC DRUG LABEL
Date: 20260112

ACTIVE INGREDIENTS: SUS SCROFA ADRENAL GLAND 6 [hp_X]/1 g; THYROID, BOVINE 8 [hp_X]/1 g; SOMATROPIN 30 [hp_X]/1 g
INACTIVE INGREDIENTS: WATER; PHENOXYETHANOL; CAPRYLYL GLYCOL; SORBIC ACID; ALOE VERA LEAF; GREEN TEA LEAF; CARBOMER INTERPOLYMER TYPE A (ALLYL SUCROSE CROSSLINKED); LICORICE; CHASTE TREE; EPIMEDIUM SAGITTATUM TOP; GINKGO; MUCUNA PRURIENS SEED; DIOSCOREA VILLOSA TUBER; SODIUM HYDROXIDE; ASCORBIC ACID; POLYETHYLENE GLYCOL 1500; PEG-8 DIMETHICONE; POLYETHYLENE GLYCOL 700; TOCOPHEROL; EDETATE DISODIUM; OREGANO; POTASSIUM SORBATE

Drug Facts:

ACTIVE INGREDIENTS:

Somatropin 30X, Glandula Suprarenalis Suis 6X, Thyroidinum (Bovine) 8X.

INDICATIONS:

May Improve Bone and Joint Health*
May Increase Muscle and Reduce Fat*
May Improve Sleep*

*These statements have not been evaluated by the FDA

WARNINGS:

WARNING: KEEP OUT OF REACH OF CHILDREN

If swallowed, get medical help or contact a Poison Control Center right away.

If pregnant or breast-feeding, ask a health professional before use.

FOR EXTERNAL USE ONLY

Sealed for your protection.

Do not use if seal has been broken or tampered with.

KEEP OUT OF REACH OF CHILDREN:

If swallowed, get medical help or contact a Poison Control Center right away.

DIRECTIONS:

Apply two full pumps in the morning and two full pumps in the evening: five days on, two days off. For intensive use, apply four full pumps in the morning, four full pumps in the evening. Gel should always be applied to the thin areas of skin, wherever veins are visible. You may apply the gel to your underarms, forearms, wrists and behind the knees. Applied locations should be rotated. Store between 48-78 degrees, in a cool dry place away from sunlight.

INDICATIONS:

May Improve Bone and Joint Health*
May Increase Muscle and Reduce Fat*
May Improve Sleep*

*These statements have not been evaluated by the FDA

INACTIVE INGREDIENTS:

Purified Water, Phenoxyethanol & Caprylyl Glycol & Sorbic Acid, Aloe Barbadensis Leaf, Camellia Sinensis (Green Tea) Leaf, Acrylates/C10-30 Alkyl Acrylate Crosspolymer, Glycyrrhiza Glabra (Licorice) Root, Vitex Agnus-castus (Chaste Tree) Fruit, Epimedium Sagittatum (Epimedium) Leaf, Ginkgo Biloba (Ginkgo) Leaf, Mucuna Pruriens (Velvet Bean) Seed, Dioscorea Villosa (Wild Yam) Root, Sodium Hydroxide, Ascorbic Acid, Peg-33 (and) Peg-8 Dimethicone, (and) Peg-14, Aloe Vera Leaf Juice, Tocopherols (Soy), Edetate Disodium, Natural Plant Extract, Potassium Sorbate.

QUESTIONS:

Manufactured for:
New U Life
2623 Pleasant Hill Rd,
Pleasant Hill, CA 94523
1.925.274.5000

SOMADERM
is a licensed
trademark of XygenyXTM

PACKAGE LABEL DISPLAY:

NEW U LIFE
SOMADERM
MAXIMUM STRENGTH
SOMATROPIN
HOMEOPATHIC
TRANSDERMAL GEL
NET WT 3.4oz (96g)